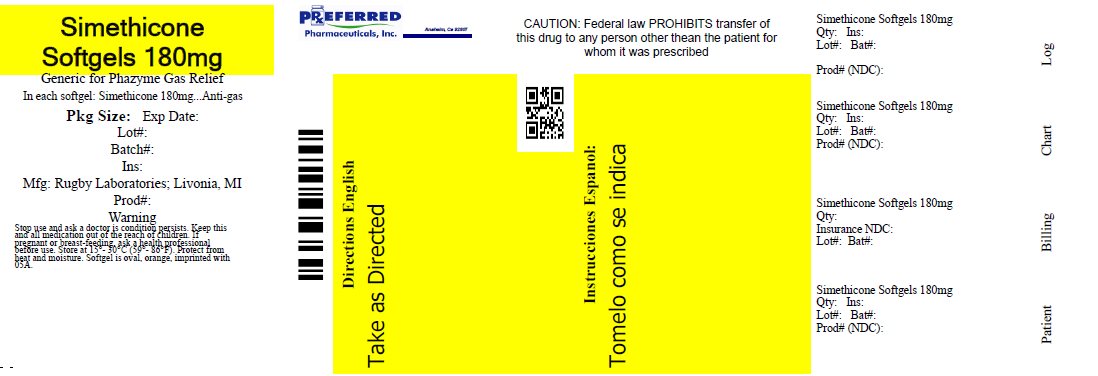 DRUG LABEL: Gas Relief
NDC: 68788-7890 | Form: CAPSULE, LIQUID FILLED
Manufacturer: Preferred Pharmaceuticals Inc.
Category: otc | Type: HUMAN OTC DRUG LABEL
Date: 20250922

ACTIVE INGREDIENTS: DIMETHICONE, UNSPECIFIED 180 mg/1 1
INACTIVE INGREDIENTS: FD&C YELLOW NO. 6; GELATIN, UNSPECIFIED; GLYCERIN; FD&C RED NO. 40

Drug Facts

Active ingredient (in each softgel)

Simethicone 180 mg

Purpose

Antigas

Uses

- relieves bloating, pressure, or fullness commonly referred to as gas

Warnings

Stop use and ask a doctor if

condition persists.

If pregnant or breast-feeding,

ask a health professional before use.

Directions

- swallow one or two softgels as symptoms occur
- do not exceed two softgels per 24 hours except under the advice and supervision of a physician

Other information

- store between 15-30ºC (59-86ºF)
- protect from heat and moisture

Inactive ingredients

FD&C red #40, FD&C yellow #6, gelatin, glycerin

Questions or comments?

Call 1-800-645-2158

Principal Display Panel

Compare to the active ingredient in Phazyme® Ultra Strength†

Ultra Strength

Simethicone 180 mg

Antigas

Fast relief of

- Gas
- Pressure
- Bloating
- Discomfort

†This product is not manufactured or distributed by C.B. Fleet Company Inc., distributor of Phazyme® Ultra Strength

TAMPER EVIDENT: DO NOT USE IF PRINTED SAFETY SEAL UNDER CAP IS BROKEN OR MISSING

Distributed by:

RUGBY® LABORATORIES

17177 N Laurel Park Drive,

Suite 233

Livonia, MI 48152

Error! Hyperlink reference not valid.

.

Product Label

RUGBY LABORATORIES Ultra Strength Simethicone